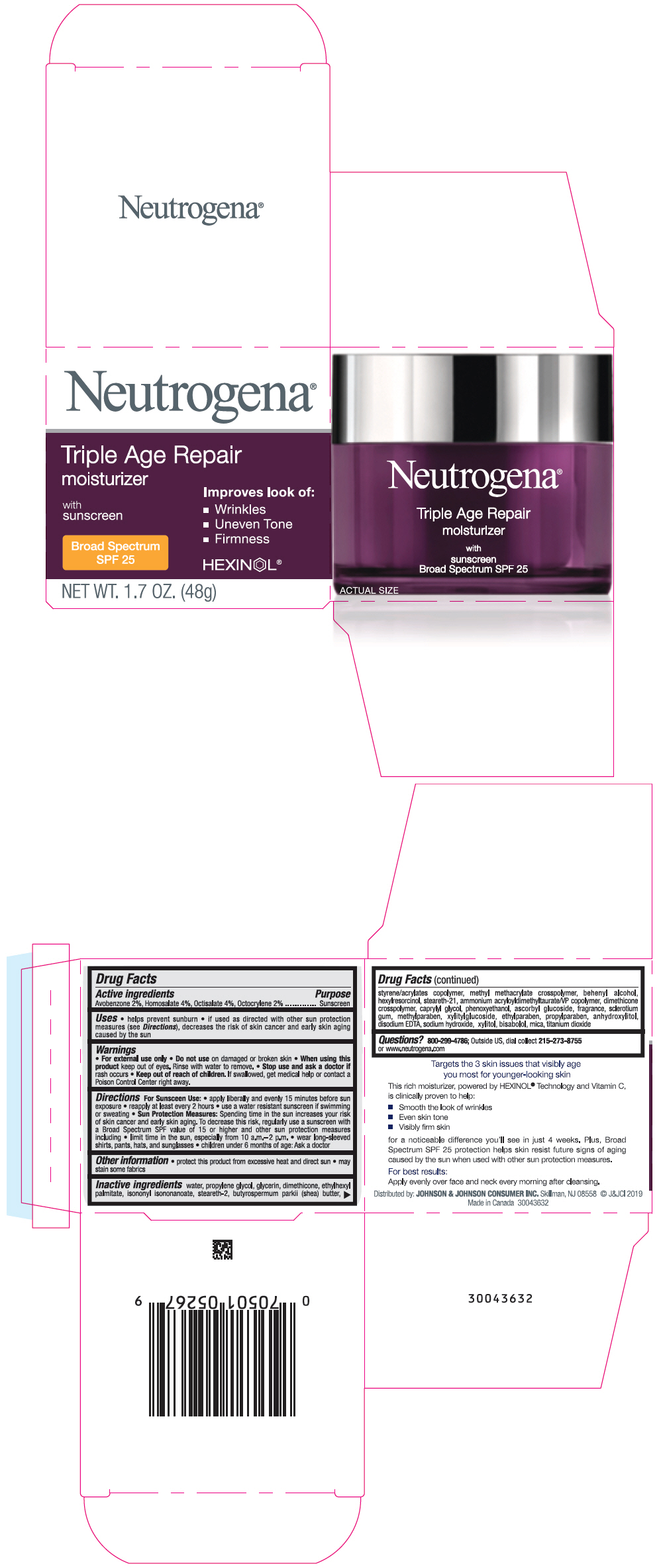 DRUG LABEL: Neutrogena Triple Age Repair Moisturizer with Sunscreen Broad Spectrum SPF 25
NDC: 69968-0414 | Form: CREAM
Manufacturer: Kenvue Brands LLC
Category: otc | Type: HUMAN OTC DRUG LABEL
Date: 20250821

ACTIVE INGREDIENTS: AVOBENZONE 20 mg/1 g; HOMOSALATE 40 mg/1 g; OCTISALATE 40 mg/1 g; OCTOCRYLENE 20 mg/1 g
INACTIVE INGREDIENTS: BUTYL METHACRYLATE/METHYL METHACRYLATE/METHACRYLIC ACID/STYRENE CROSSPOLYMER; WATER; PROPYLENE GLYCOL; GLYCERIN; DIMETHICONE; ETHYLHEXYL PALMITATE; ISONONYL ISONONANOATE; STEARETH-2; SHEA BUTTER; METHYL METHACRYLATE/GLYCOL DIMETHACRYLATE CROSSPOLYMER; DOCOSANOL; HEXYLRESORCINOL; STEARETH-21; AMMONIUM ACRYLOYLDIMETHYLTAURATE/VP COPOLYMER; DIMETHICONE CROSSPOLYMER (450000 MPA.S AT 12% IN CYCLOPENTASILOXANE); CAPRYLYL GLYCOL; PHENOXYETHANOL; ASCORBYL GLUCOSIDE; BETASIZOFIRAN; METHYLPARABEN; XYLITYLGLUCOSIDE; ETHYLPARABEN; PROPYLPARABEN; ANHYDROXYLITOL; EDETATE DISODIUM ANHYDROUS; SODIUM HYDROXIDE; XYLITOL; LEVOMENOL; MICA; TITANIUM DIOXIDE

Neutrogena® Triple Age Repair moisturizer with sunscreen Broad Spectrum SPF 25

Drug Facts

ACTIVE INGREDIENT

Active ingredients | Purpose
Avobenzone (2%) | Sunscreen
Homosalate (4%) | Sunscreen
Octisalate (4%) | Sunscreen
Octocrylene (2%) | Sunscreen

Uses

- helps prevent sunburn
- if used as directed with other sun protection measures (see Directions), decreases the risk of skin cancer and early skin aging caused by the sun

Warnings

- For external use only

- Do not use on damaged or broken skin

- When using this product keep out of eyes. Rinse with water to remove.

- Stop use and ask a doctor if rash occurs

- Keep out of reach of children. If swallowed, get medical help or contact a Poison Control Center right away.

Directions

For Sunscreen Use:

- apply liberally and evenly 15 minutes before sun exposure
- reapply at least every 2 hours
- use a water resistant sunscreen if swimming or sweating
- Sun Protection Measures: Spending time in the sun increases your risk of skin cancer and early skin aging. To decrease this risk, regularly use a sunscreen with a Broad Spectrum SPF value of 15 or higher and other sun protection measures including:
  - limit time in the sun, especially from 10 a.m. – 2 p.m.
  - wear long-sleeved shirts, pants, hats, and sunglasses
  - children under 6 months of age: Ask a doctor

Other Information

- protect this product from excessive heat and direct sun
- may stain some fabrics

Inactive ingredient

water, propylene glycol, glycerin, dimethicone, ethylhexyl palmitate, isononyl isononanoate, steareth-2, butyrospermum parkii (shea) butter, styrene/acrylates copolymer, methyl methacrylate crosspolymer, behenyl alcohol, hexylresorcinol, steareth-21, ammonium acryloyldimethyltaurate/VP copolymer, dimethicone crosspolymer, caprylyl glycol, phenoxyethanol, ascorbyl glucoside, fragrance, sclerotium gum, methylparaben, xylitylglucoside, ethylparaben, propylparaben, anhydroxylitol, disodium EDTA, sodium hydroxide, xylitol, bisabolol, mica, titanium dioxide

Questions?

800-299-4786; or Outside US, dial collect 215-273-8755 or www.neutrogena.com

Distributed by: JOHNSON & JOHNSON CONSUMER INC. Skillman, NJ 08558

PRINCIPAL DISPLAY PANEL - 48 g Jar Carton

Neutrogena®

Triple Age Repair
moisturizer

with
sunscreen
Broad Spectrum
SPF 25

Improves look of:

- Wrinkles
- Uneven Tone
- Firmness

HEXINOL®

NET WT. 1.7 OZ. (48g)